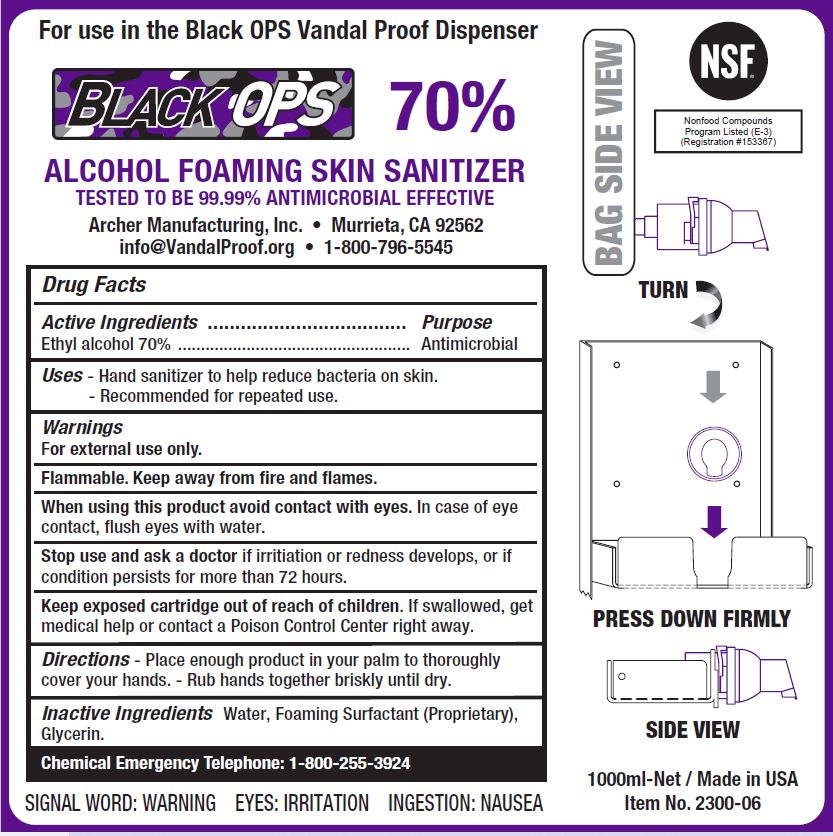 DRUG LABEL: BLACK OPS 70 PERCENT ALCOHOL FOAMING SKIN SANITIZER
NDC: 79016-102 | Form: SOLUTION
Manufacturer: Archer Manufacturing, Inc.
Category: otc | Type: HUMAN OTC DRUG LABEL
Date: 20241205

ACTIVE INGREDIENTS: ALCOHOL 70 mL/100 mL
INACTIVE INGREDIENTS: GLYCERIN; WATER

ARCHER - BLACK OPS 70% ALCOHOL FOAMING SKIN SANITIZER (79016-102)

ACTIVE INGREDIENTS

ETHYL ALCOHOL 70%

PURPOSE

ANTIMICROBIAL

USES

- HAND SANITIZER TO HELP REDUCE BACTERIA ON THE SKIN.
- RECOMMENDED FOR REPEATED USE.

WARNINGS

FOR EXTERNAL USE ONLY.

FLAMMABLE. KEEP AWAY FROM FIRE AND FLAMES.

WHEN USING THIS PRODUCT AVOID CONTACT WITH EYES. IN CASE OF EYE CONTACT, FLUSH WITH WATER.

STOP USE AND ASK A DOCTOR IF IRRITATION OR REDNESS DEVELOPS, OR IF CONDITION PERSISTS FOR MORE THAN 72 HOURS.

KEEP OUT OF REACH OF CHILDREN

KEEP EXPOSED CARTRIDGE OUT OF REACH OF CHILDREN. IF SWALLOWED, GET MEDICAL HELP OR CONTACT POISON CONTROL RIGHT AWAY.

DIRECTIONS

- PLACE ENOUGH PRODUCT IN YOUR PALM TO THOROUGHLY COVER YOUR HANDS.
- RUB HANDS TOGETHER BRISKLY UNTIL DRY.

INACTIVE INGREDIENTS

WATER, FOAMING SURFACTANT (PROPRIETARY), GLYCERIN.